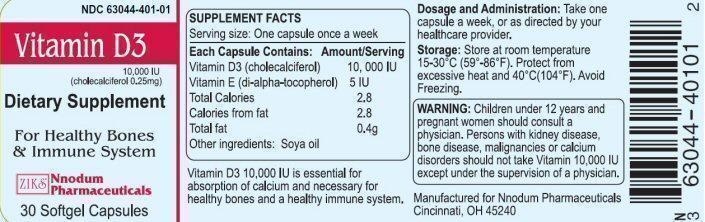 DRUG LABEL: Vitamin D3
NDC: 63044-401 | Form: CAPSULE, GELATIN COATED
Manufacturer: Nnodum Pharmaceuticals
Category: other | Type: DIETARY SUPPLEMENT
Date: 20251229

ACTIVE INGREDIENTS: CHOLECALCIFEROL 0.25 mg/1 1; .ALPHA.-TOCOPHEROL 5 [iU]/1 1
INACTIVE INGREDIENTS: SOYBEAN OIL

Statement of Identity

Vitamin D3 10,000 iu is essential for absorption of calcium and necessary for healthy bones and a healthy immune system.

Warning

Children under 12 years and pregnant women should consult a physician.

Dosage and Administration:

Serving Size: One capsule once a week.

Take one capsule a week or as directed by your health care provider.

Each Capsule Contains: Amount/Serving

Vitamin D3 (cholecalciferol) 10,000 IU

Vitamin E (di-alpha-tocopherol) 5 IU

Total Calories 2.8

Calories from fat 2.8

Total fat 0.4g

Other ingredients: Soya oil

Precautions/Warning

Persons with kidney disease, bone disease, malignancies or calcium disorders should not take Vitamin 10,000 IU except under the supervision of a physician.

Storage

Store at room temperature 15-30° C (59-86° F). Protect from excessive heat and 40° C(104° F) Avoid Freezing.

Health Claim

For Healthy Bones and Immune System

Vitamin D3 Product Label

NDC 63044-401-01
Vitamin D3
10,000 IU (cholecalciferol 0.25mg)
Dietary Supplement
For Healthy Bones and Immune System
Nnodum Pharmaceuticals
30 Softgel Capsules
Manufactured for Nnodum Pharmaceuticals
Cincinnati, OH 45240

res